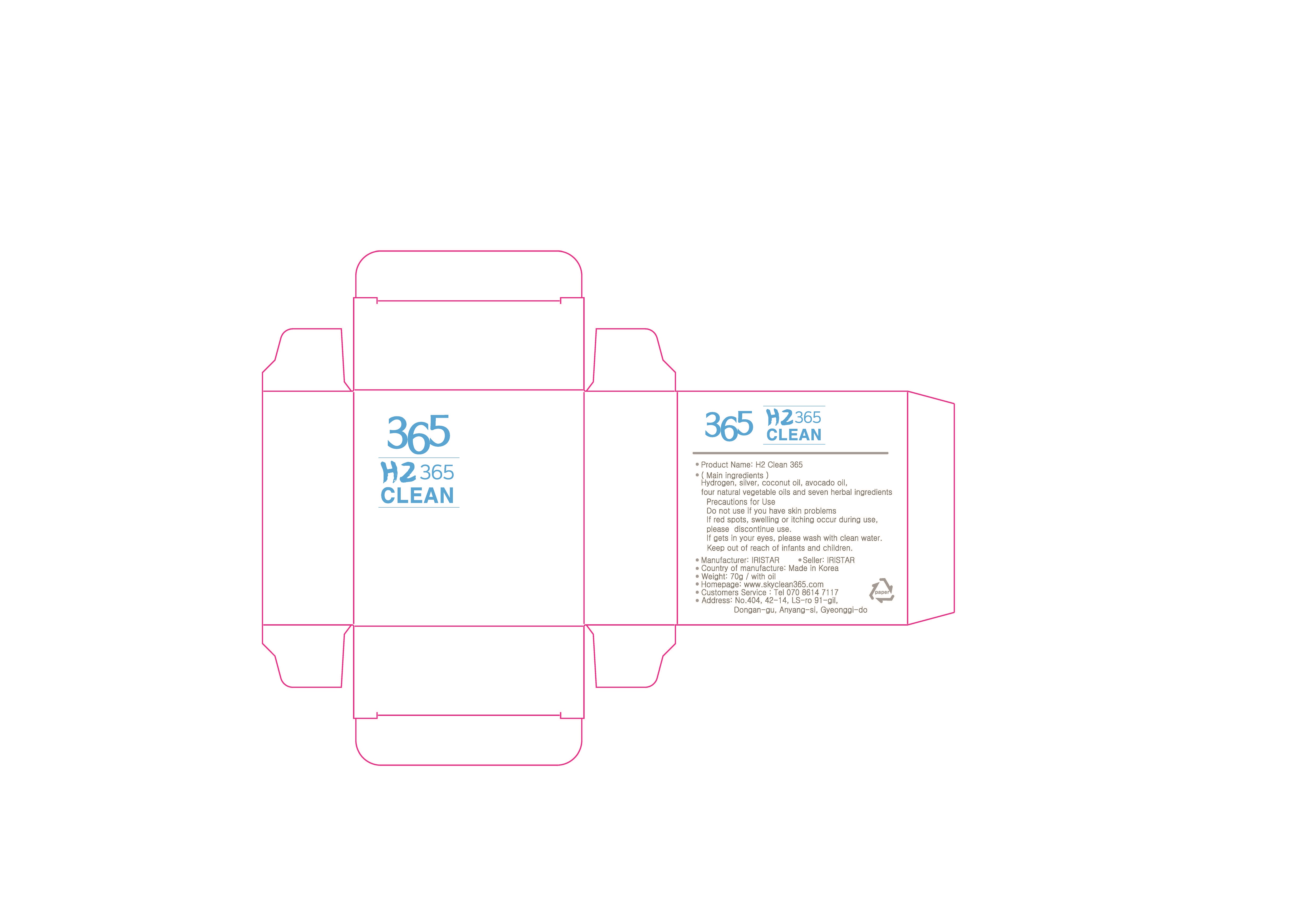 DRUG LABEL: H2 365 CLEAN
NDC: 73269-0001 | Form: SOAP
Manufacturer: IRISTA
Category: otc | Type: HUMAN OTC DRUG LABEL
Date: 20190916

ACTIVE INGREDIENTS: GLYCERIN 5 g/100 g
INACTIVE INGREDIENTS: COCONUT OIL

Drug Facts

ACTIVE INGREDIENT

glycerin

INACTIVE INGREDIENT

coconut oil powder, silver, raisinseed oil, avocado oil, plumseed oil

PURPOSE

skin protectant

keep out of reach of the children

INDICATIONS AND USAGE

apply to the skin and wash away with clean water

do not use if yu have skin problems

if red spots, swelling or itching occur during use, discontinue use

if gets in your eyes, wash with clean water

DOSAGE AND ADMINISTRATION

for external use only